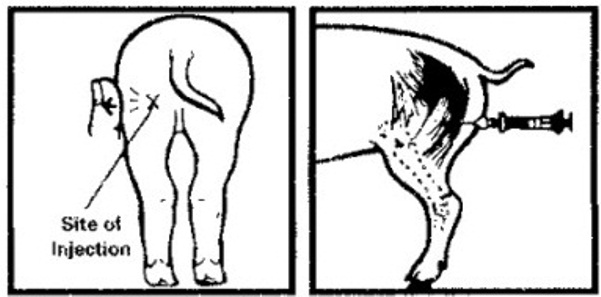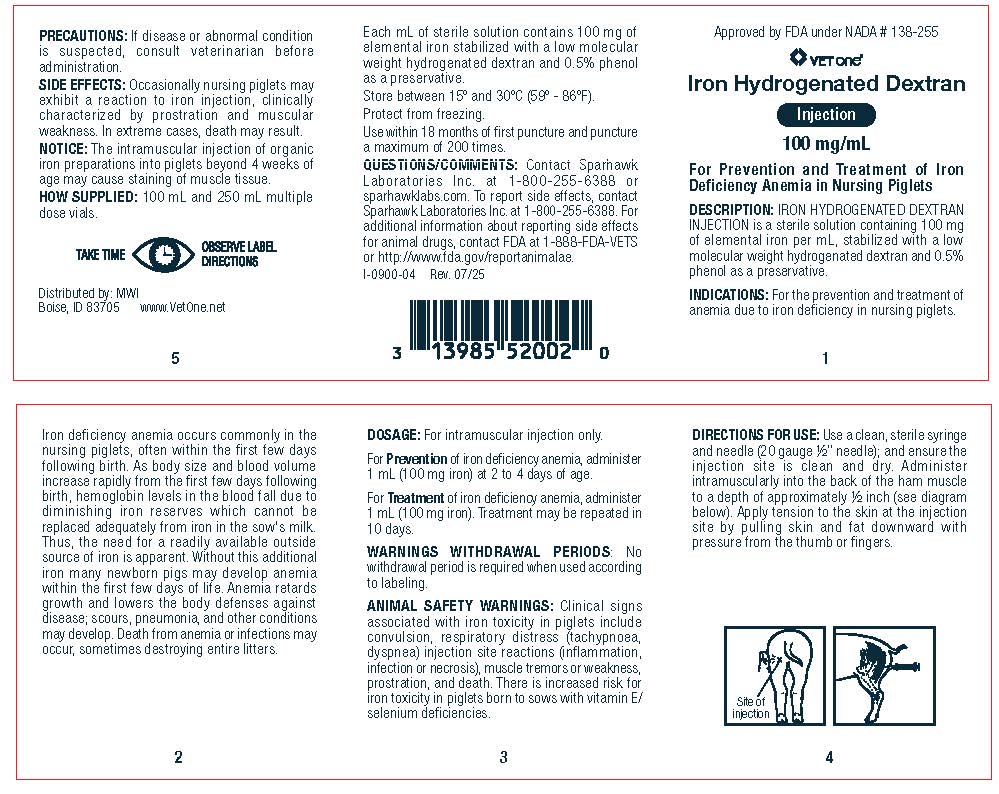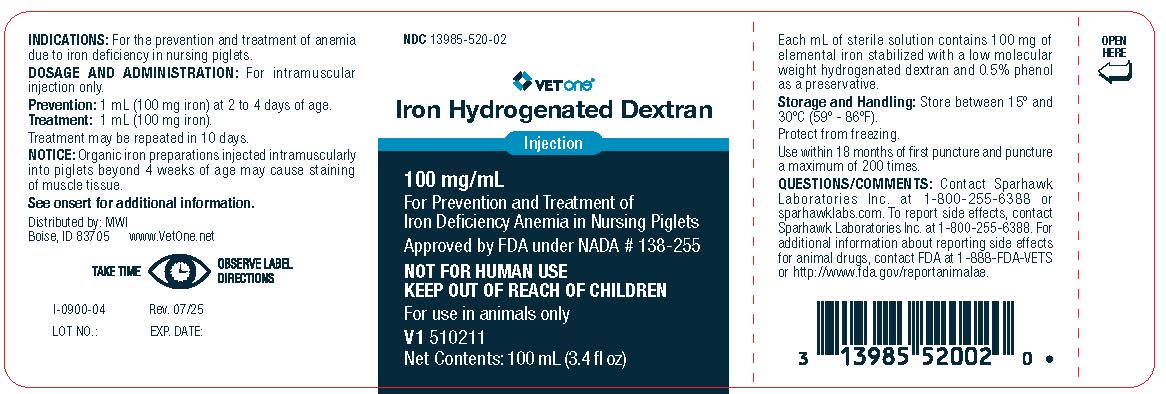 DRUG LABEL: IRON HYDROGENATED DEXTRAN
NDC: 13985-520 | Form: INJECTION
Manufacturer: MWI Veterinary Supply, Inc.
Category: animal | Type: OTC ANIMAL DRUG LABEL
Date: 20251002

ACTIVE INGREDIENTS: IRON 100  mg/1 mL

IRON HYDROGENATED DEXTRAN INJECTION

DESCRIPTION

100 mg/mL

For Prevention and Treatment of Iron Deficiency Anemia in Nursing Piglets

Approved by FDA under NADA # 138-255

NOT FOR HUMAN USE

KEEP OUT OF REACH OF CHILDREN

DESCRIPTION: IRON HYDROGENATED DEXTRAN INJECTION is a sterile solution containing 100 mg of elemental iron per mL, stabilized with a low molecular weight hydrogenated dextran and 0.5% phenol as a preservative.

INDICATIONS

For the prevention and treatment of anemia due to iron deficiency in nursing piglets. Iron deficiency anemia occurs commonly in the nursing piglets, often within the first few days following birth. As body size and blood volume increase rapidly from the first few days following birth, hemoglobin levels in the blood fall due to diminishing iron reserves which cannot be replaced adequately from iron in the sow's milk. Thus, the need for a readily available outside source of iron is apparent. Without this additional iron many newborn pigs may develop anemia within the first few days of life. Anemia retards growth and lowers the body defenses against disease; scours, pneumonia, and other conditions may develop. Death from anemia or infections may occur, sometimes destroying entire litters.

DOSAGE

For intramuscular injection only.

For Prevention of iron deficiency anemia, administer 1 mL (100 mg iron) at 2 to 4 days of age.

For Treatment of iron deficiency anemia, administer 1 mL (100 mg iron). Treatment may be repeated in 10 days.

DIRECTIONS FOR USE

Use a clean, sterile syringe and needle (20 gauge ½” needle); and ensure the injection site is clean and dry. Administer intramuscularly into the
back of the ham muscle to a depth of approximately ½ inch (see diagram below). Apply tension to the skin at the injection site by pulling skin and fat downward withpressure from the thumb or fingers.

PRECAUTIONS

If disease or abnormal condition is suspected, consult veterinarian before administration.

WARNINGS

WARNINGS WITHDRAWAL PERIODS: No withdrawal period is required when used according to labeling.

ANIMAL SAFETY WARNINGS: Clinical signs associated with iron toxicity in piglets include convulsion, respiratory distress (tachypnoea, dyspnea) injection site reactions (inflammation, infection or necrosis), muscle tremors or weakness, prostration, and death. There is increased risk for iron toxicity in piglets born to sows with vitamin E/ selenium deficiencies.

SIDE EFFECTS

Occasionally nursing piglets may exhibit a reaction to iron injection, clinically characterized by prostration and muscular weakness. In extreme cases, death may result.

NOTICE: The intramuscular injection of organic iron preparations into pigs beyond 4 weeks of age may cause staining of muscle tissue.

HOW SUPPLIED

100 mL and 250 mL multiple dose vials.

Each mL of sterile solution contains 100 mg of elemental iron stabilized with a low molecular weight hydrogenated dextran and 0.5% phenol as a preservative.

STORAGE AND HANDLING

Store between 15º and 30ºC (59º - 86ºF).
Protect from freezing.
Use within 18 months of first puncture and
puncture a maximum of 200 times.

QUESTIONS/COMMENTS

Contact Sparhawk Laboratories Inc. at 1-800-255-6388 or sparhawklabs.com. To report side effects, contact Sparhawk Laboratories Inc. at 1-800-255-6388. For additional information about reporting side effects for animal drugs, contact FDA at 1-888-FDA-VETS or
http://www.fda.gov/reportanimalae.